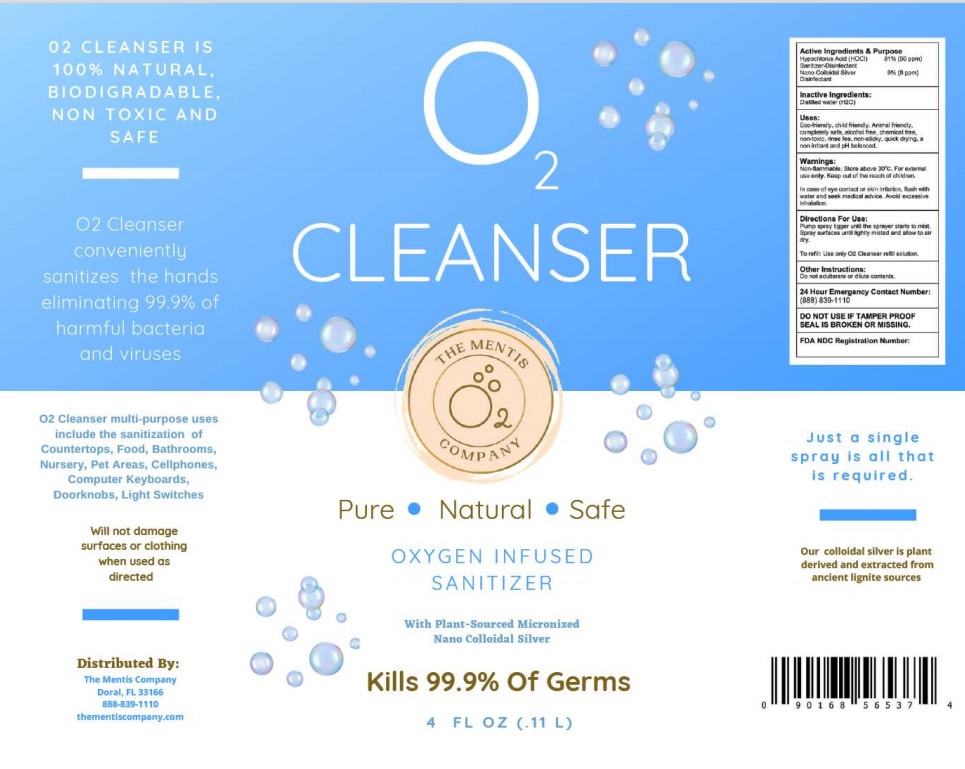 DRUG LABEL: OXICLEANSE
NDC: 72136-008 | Form: SPRAY
Manufacturer: Oxigenesis, Inc.
Category: otc | Type: HUMAN OTC DRUG LABEL
Date: 20210301

ACTIVE INGREDIENTS: HYPOCHLOROUS ACID 50 [ppm]/1 mL; SILVER 8 [ppm]/1 mL
INACTIVE INGREDIENTS: WATER

Active Ingredient

Hypochlorus Acid (HOCl) 81% (50 ppm)......... Sanitizer, disinfectant

Nano Colloidal Silve 9% (8 ppm) ......... Disinfectant

Purpose

Sanitizer, Disinfectant

Uses

Eco-friendly, child-friendly, animal friendly, completely safe, alcohol free, chemical free, non-toxic, rinse free, non-sticky, quick drying, a non-irritant and pH balanced.

Warnings

- Warnings: Non-flammable. Store above 30º C. For external use only.
- Keep out of the reach of children.
- In case of eye contact or skin irritation, flush with water and seek medical advice.
- Avoid excessive inhalation.

Directions

Pump spray trigger to build pressure and hold. Spray surfaces until lightly misted and allow to air dry.
To refill: use only OxiCleanse™ refill solution.

Other information

Do not adulterate or dilute content.

24 Hour Emergency Contact Number: (888) 839-1110

DO NOT USE IF TAMPER PROOF SEAL IS BROKEN OR MISSING.

Inactive ingredients

Distilled water (H2O)